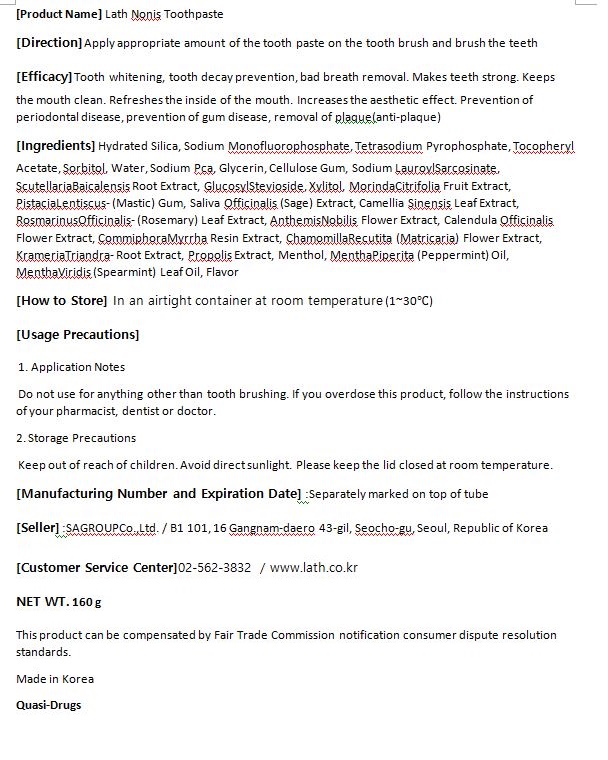 DRUG LABEL: Lath NonisToothpaste
NDC: 82351-0001 | Form: PASTE
Manufacturer: SA Group Co Ltd
Category: otc | Type: HUMAN OTC DRUG LABEL
Date: 20211104

ACTIVE INGREDIENTS: SODIUM MONOFLUOROPHOSPHATE 0.65 g/100 g
INACTIVE INGREDIENTS: GLYCERIN; SORBITOL

ACTIVE INGREDIENT

SODIUM MONOFLUOROPHOSPHATE

INACTIVE INGREDIENT

HYDRATED SILICA
TETRASODIUM PYROPHOSPHATE
TOCOPHERYL ACETATE
SORBITOL
SODIUM PCA
GLUCOSYL STEVIOSIDE
XYLITOL
GLYCERIN
CELLULOSE GUM
SODIUM LAUROYL SARCOSINATE
SCUTELLARIA BAICALENSIS ROOT EXTRACT
MORINDA CITRIFOLIA FRUIT EXTRACT
PISTACIA LENTISCUS (MASTIC) GUM
SALIVA OFFICINALIS (SAGE) EXTRACT
CAMELLIA SINENSIS LEAF EXTRACT
ROSMARINUS OFFICINALIS (ROSEMARY) LEAF EXTRACT
ANTHEMIS NOBILIS FLOWER EXTRACT
CALENDULA OFFICINALIS FLOWER EXTRACT
COMMIPHORA MYRRHA RESIN EXTRACT
CHAMOMILLA RECUTITA (MATRICARIA) FLOWER EXTRACT
KRAMERIA TRIANDRA ROOT EXTRACT
PROPOLIS EXTRACT
MENTHOL
MENTHA PIPERITA (PEPPERMINT) OIL
MENTHA VIRIDIS (SPEARMINT) LEAF OIL
FLAVOR
FLAVOR
WATER

PURPOSE

Tooth whitening, tooth decay prevention, bad breath removal. Makes teeth strong. Keeps the mouth clean. Refreshes the inside of the mouth. Increases the aesthetic effect. Prevention of periodontal disease, prevention of gum disease, removal of plaque(anti-plaque)

KEEP OUT OF REACH OF CHILDREN

WARNING

For oral use only
When using this product

■ Do not use other than brushing teeth and be careful not to swallow

Keep out of reach of children

■ if swallowed, seek medical help or contact the poison control center immediately

USES

for oral use only

INDICATION & USAGE SECTION

Brush thoroughly ofter each meal or at least twice a day, as directed by yourdoctorordendst
Do not swallow.

Do not use if seal is broken or missing.

store in a cool, dry place.